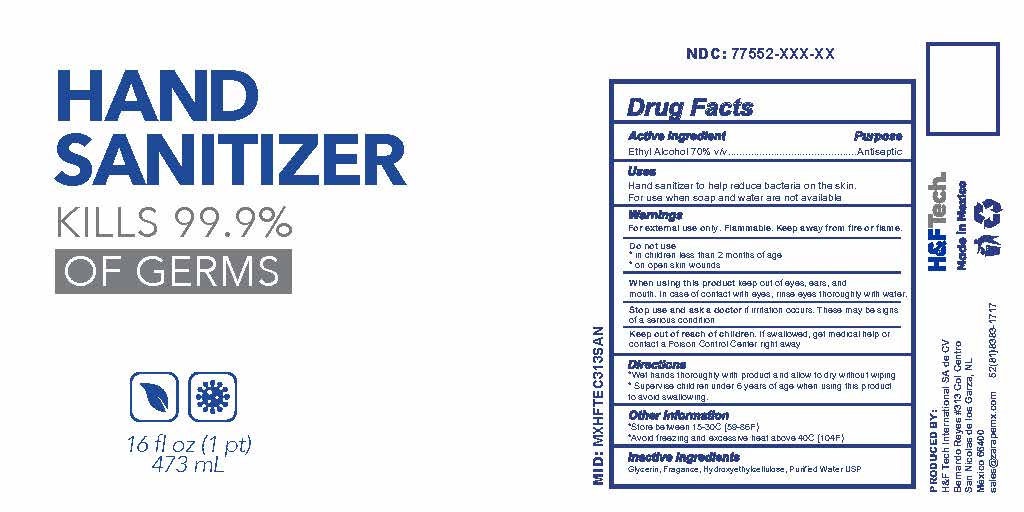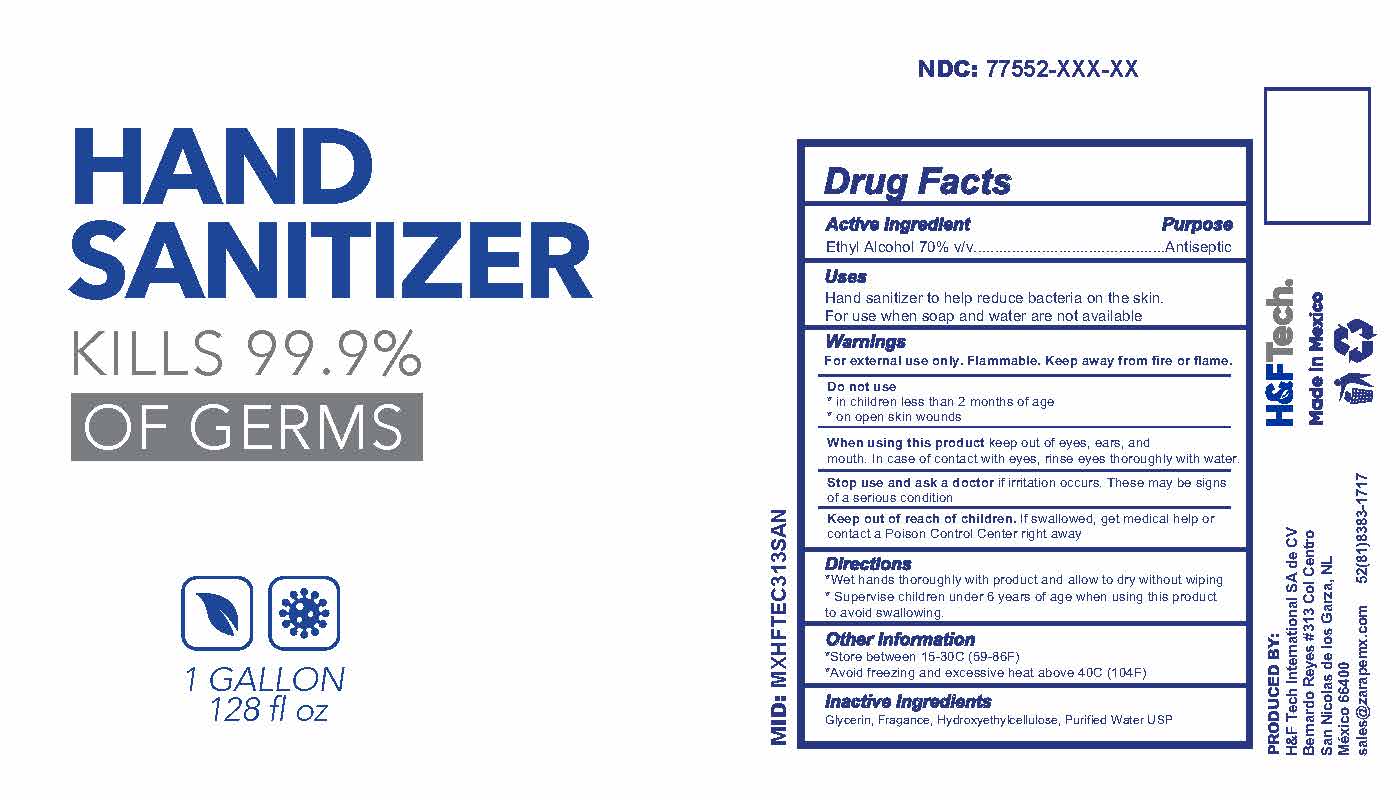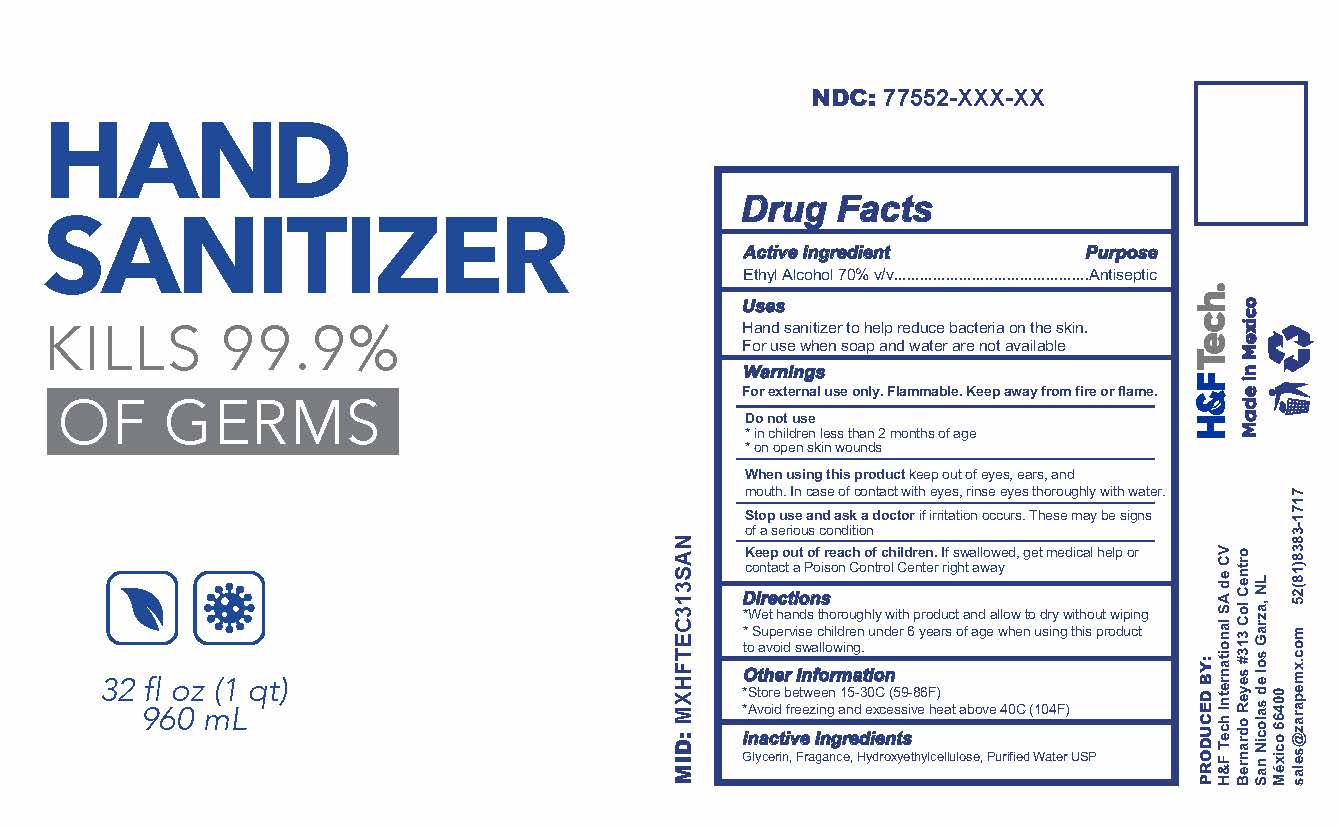 DRUG LABEL: Hand Sanitizer
NDC: 77552-005 | Form: GEL
Manufacturer: H&F TECH INTERNATIONAL, S.A. DE C.V.
Category: otc | Type: HUMAN OTC DRUG LABEL
Date: 20200625

ACTIVE INGREDIENTS: ALCOHOL 70 mL/100 mL
INACTIVE INGREDIENTS: HYDROXYETHYL CELLULOSE, UNSPECIFIED; GLYCERIN; WATER

H&F TECH INTERNATIONAL, S.A. DE C.V.

Active Ingredient(s)

Alcohol 70% v/v. Purpose: Antiseptic

Purpose

Antiseptic

Use

Hand Sanitizer to help reduce bacteria on the skin. For use when soap and water are not available.

Warnings

For external use only. Flammable. Keep away from heat or flame

Do not use

- in children less than 2 months of age
- on open skin wounds

When using this product keep out of eyes, ears, and mouth. In case of contact with eyes, rinse eyes thoroughly with water.
Stop use and ask a doctor if irritation or rash occurs. These may be signs of a serious condition.
Keep out of reach of children. If swallowed, get medical help or contact a Poison Control Center right away.

Stop use and ask a doctor if irritation or rash occurs. These may be signs of a serious condition.

Keep out of reach of children. If swallowed, get medical help or contact a Poison Control Center right away.

Directions

- Wet hands thoroughly with product and allow to dry without wiping.
- Supervise children under 6 years of age when using this product to avoid swallowing.

Inactive ingredients

Glycerin, Fragrance, Hydroxyethylcellulose, Purified Water USP

Other information

- Store between 15-30C (59-86F)
- Avoid freezing and excessive heat above 40C (104F)

PACKAGE LABEL

473mL

PACKAGE LABEL

960mL